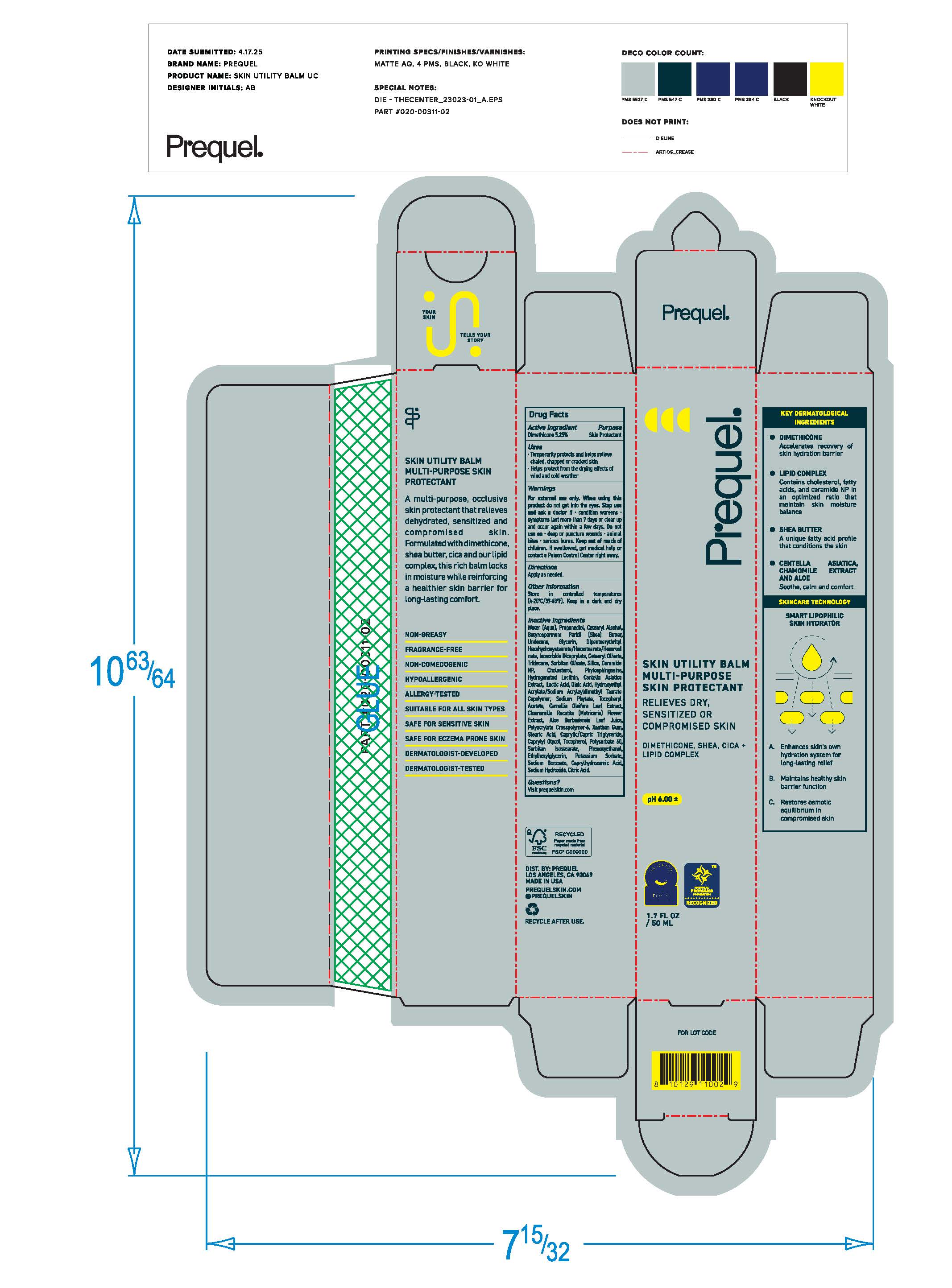 DRUG LABEL: Prequel Skin Utility Balm Multi-Purpose Skin Protectant
NDC: 82800-060 | Form: OINTMENT
Manufacturer: The Center Brands, LLC
Category: otc | Type: HUMAN OTC DRUG LABEL
Date: 20251204

ACTIVE INGREDIENTS: DIMETHICONE 5.25 mg/1 g
INACTIVE INGREDIENTS: WATER; PROPANEDIOL; BUTYROSPERMUM PARKII (SHEA) BUTTER UNSAPONIFIABLES; UNDECANE; DIPENTAERYTHRITYL HEXASTEARATE; GLYCERIN; ISOSORBIDE DICAPRYLATE; CETEARYL OLIVATE; SILICON DIOXIDE; PHENOXYETHANOL; ETHYLHEXYLGLYCERIN; CERAMIDE NP; CHOLESTEROL; PHYTOSPHINGOSINE; HYDROGENATED SOYBEAN LECITHIN; CENTELLA ASIATICA; SODIUM ACRYLATE/SODIUM ACRYLOYLDIMETHYLTAURATE COPOLYMER (4000000 MW); AMMONIUM ACRYLOYLDIMETHYLTAURATE/VP COPOLYMER; HYDROGENATED POLYDECENE TYPE I; XANTHAN GUM; STEARIC ACID; HEXASODIUM PHYTATE; CAMELLIA OLEIFERA LEAF; CHAMOMILE FLOWER OIL; ALOE VERA LEAF; CITRIC ACID ACETATE; LACTIC ACID; OLEIC ACID; LAURETH-8; CAPRYLYL GLYCOL; CAPRYLHYDROXAMIC ACID; TOCOPHEROL; POTASSIUM SORBATE; SODIUM BENZOATE; SODIUM SULFATE; TERT-BUTYL ACETATE

DRUG FACTS

Purpose

Skin Protectant

Active Ingredients

Dimethicone 5.25%

Uses

Temporarily protects and helps releive chafed, chapper or cracked skin

Helps protect fomr the drying effects of wind and cold weather

Warnings

Fox external use only.

When using this product do not get into eyes

Stop use and ask a doctor if condition worsens

symptoms last more than 7 days or clear up and occur again within a few days

Keep out of reach of children. If swallowed, get medical help or contact a Poison Control Center right away.

Directions

Apply as needed.

Inactive ingredients

Water (Aqua), Propanediol, Cetearyl Alcohol, Butyrospermum Parkii (Shea) Butter, Undecane, Glycerin, Dipentaerythryityl Hexahydrostearate/Hexastearate/Hexarosinate, Isosorbate Dicaprylate, Cetearyl Olivate, Tridecane, Sorbitan Olivate, Silica, Ceramide NP, Cholesterol, Phytospingosine, Hydrogentaed Lecithin, Centella Asiatica Extract, Sodium Acrylate/Sodium Acryloyldimethyl Taurate Copolymer, Ammonium Acryloyldimethyltuarate/VP Copolymer, Hydrogenated Polydecene, Xanthan Gum, Stearic Acid, Sodium Phytate, Tocopheryl Acetate, Camomilla Recutita Flower Extract, Aloe Barbadensis Leaf Juice, Phenoxyethanol, Ethylhexylglycerin, Citric Acid, Caprylic/Capric Trigylceride, Lactic Acid, Oleic Acid, Laureth-8, Caprylyl Glycol, Caprylhydroxamic Acid, Tocopherol, Potassium Sorbate, Sodium Benzoate, Sodium Sulfate, t-Butyl Acohol

Other Information

• Store in controlled temperatures (4-20°C/39-68°F). Keep in a dark and dry place.

Questions?

Visit prequelskin.com